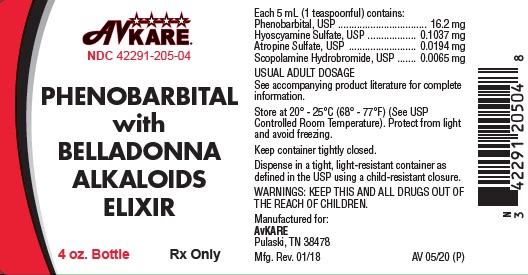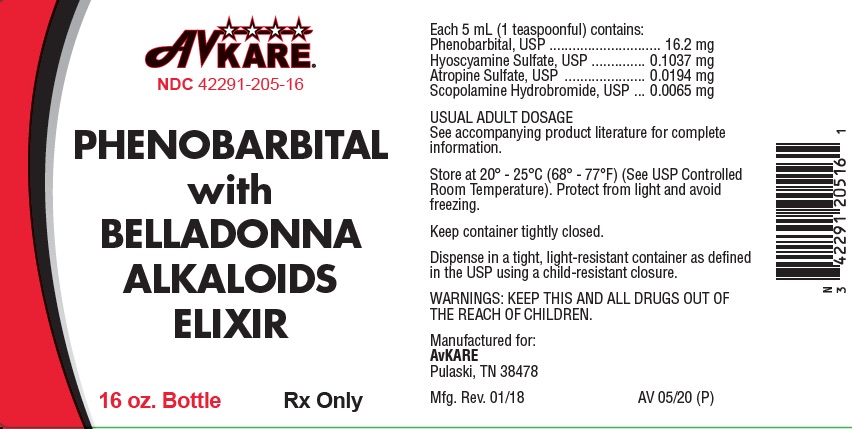 DRUG LABEL: PHENOBARBITAL WITH BELLADONNA ALKALOIDS
NDC: 42291-205 | Form: ELIXIR
Manufacturer: AvKARE
Category: prescription | Type: HUMAN PRESCRIPTION DRUG LABEL
Date: 20200805

ACTIVE INGREDIENTS: PHENOBARBITAL 16.2 mg/5 mL; HYOSCYAMINE SULFATE 0.1037 mg/5 mL; ATROPINE SULFATE 0.0194 mg/5 mL; SCOPOLAMINE HYDROBROMIDE 0.0065 mg/5 mL
INACTIVE INGREDIENTS: ALCOHOL; WATER; GLYCERIN; METHYLPARABEN SODIUM; PROPYLPARABEN SODIUM; SACCHARIN SODIUM; XYLITOL; CITRIC ACID MONOHYDRATE; REBAUDIOSIDE A

PHENOBARBITAL with BELLADONNA ALKALOIDS ELIXIR

PHENOBARBITAL with BELLADONNA ALKALOIDS ELIXIR

Rx Only

DESCRIPTION:

Each 5 mL (teaspoonful) of elixir contains:

Phenobarbital, USP ................................................... 16.2 mg

Hyoscyamine Sulfate, USP ................................... 0.1037 mg

Atropine Sulfate, USP ........................................... 0.0194 mg

Scopolamine Hydrobromide, USP ......................... 0.0065 mg

Inactive ingredients:

Ethyl Alcohol, Purified Water, Glycerin, Methylparaben Sodium, Propylparaben Sodium, Saccharin Sodium, Xylitol, Citric Acid, Stevia Reb-A, Natural and Artificial Grape Flavor

CLINICAL PHARMACOLOGY:

This drug combination provides natural belladonna alkaloids in a specific, fixed ratio combined with phenobarbital to provide peripheral anticholinergic/antispasmodic action and mild sedation.

INDICATIONS AND USAGE:

Possibly effective for use as adjunctive therapy in the treatment of irritable bowel syndrome (irritable colon, spastic colon, mucous colitis) and acute enterocolitis. May also be useful as adjunctive therapy in the treatment of duodenal ulcer.

IT HAS NOT BEEN SHOWN CONCLUSIVELY WHETHER ANTICHOLINERGIC/ANTISPASMODIC DRUGS AID IN THE HEALING OF A DUODENAL ULCER, DECREASE THE RATE OF RECURRENCES OR PREVENT COMPLICATIONS.

CONTRAINDICATIONS:

Glaucoma, obstructive uropathy (for example, bladder neck obstruction due to prostatic hypertrophy); obstructive disease of the gastrointestinal tract (as in achalasia, pyloroduodenal stenosis, etc.); paralytic ileus, intestinal atony of the elderly or debilitated patient; unstable cardiovascular status in acute hemorrhage; severe ulcerative colitis especially if complicated by toxic megacolon; myasthenia gravis; hiatal hernia associated with reflux esophagitis.

Phenobarbital with Belladonna Alkaloids Elixir is contraindicated in patients with known hypersensitivity to any of the ingredients. Phenobarbital is contraindicated in acute intermittent porphyria and in those patients in whom phenobarbital produces restlessness and/or excitement.

WARNINGS:

In the presence of a high environmental temperature, heat prostration can occur with belladonna alkaloids (fever and heatstroke due to decreased sweating). Diarrhea may be an early symptom of incomplete intestinal obstruction, especially in patients with ileostomy or colostomy. In this instance treatment with this drug would be inappropriate and possibly harmful.

Phenobarbital with Belladonna Alkaloids Elixir may produce drowsiness or blurred vision. The patient should be warned, should these occur, not to engage in activities requiring mental alertness, such as operating a motor vehicle or other machinery, and not to perform hazardous work.

Phenobarbital may decrease the effect of anticoagulants, and necessitate larger doses of the anticoagulant for optimal effect. When the phenobarbital is discontinued, the dose of the anticoagulant may have to be decreased. Phenobarbital may be habit forming and should not be administered to individuals known to be addiction prone or to those with a history of physical and/or psychological dependence upon drugs. Since barbiturates are metabolized in the liver, they should be used with caution and initial doses should be small in patients with hepatic dysfunction.

PRECAUTIONS:

General

Use with caution in patients with: autonomic neuropathy, hepatic or renal disease, hyperthyroidism, coronary heart disease, congestive heart failure, cardiac arrhythmias, tachycardia, and hypertension. Belladonna alkaloids may produce a delay in gastric emptying (antral stasis) which would complicate the management of gastric ulcer. Theoretically, with overdosage, a curare-like action may occur.

Carcinogenesis, Mutagenesis, Impairment of Fertility

Long-term studies in animals have not been performed to evaluate carcinogenic potential.

Pregnancy Category C

Animal reproduction studies have not been conducted with Phenobarbital with Belladonna Alkaloids Elixir. It is not known whether Phenobarbital with Belladonna Alkaloids Elixir can cause fetal harm when administered to a pregnant woman or can affect reproduction capacity. Phenobarbital with Belladonna Alkaloids Elixir should be given to a pregnant woman only if clearly needed.

Nursing mothers

It is not known whether this drug is excreted in human milk. Because many drugs are excreted in human milk, caution should be exercised when Phenobarbital with Belladonna Alkaloids Elixir is administered to a nursing mother.

ADVERSE REACTIONS:

Adverse reactions may include xerostomia, urinary hesitancy and retention; blurred vision; tachycardia; palpitation; mydriasis; cycloplegia; increased ocular tension; loss of taste sense; headache; nervousness; drowsiness; weakness; dizziness; insomnia; nausea; vomiting; impotence; suppression of lactation; constipation; bloated feeling; musculoskeletal pain; severe allergic reaction or drug idiosyncrasies, including anaphylaxis, urticaria and other dermal manifestations; and decreased sweating. Elderly patients may react with symptoms of excitement, agitation, drowsiness, and other untoward manifestations to even small doses of the drug. Phenobarbital may produce excitement in some patients, rather than a sedative effect. In patients habituated to barbiturates, abrupt withdrawal may produce delirium or convulsions.

To report SUSPECTED ADVERSE REACTIONS, contact AvKARE at 1-855-361-3993 or FDA at 1-800-FDA-1088 or www.fda.gov/medwatch.

DOSAGE AND ADMINISTRATION:

The dosage of Phenobarbital with Belladonna Alkaloids Elixir should be adjusted to the needs of the individual patient to assure symptomatic control with a minimum of adverse effects.

Adults:

One or two teaspoonfuls of elixir three or four times a day according to conditions and severity of symptoms.

Pediatric patients:

may be dosed every 4 to 6 hours.

Starting Dosage:

Body Weight q4h q6h

10 lb. (4.5 kg) 0.5 mL 0.75 mL

20 lb. (9.1 kg) 1.0 mL 1.5 mL

30 lb. (13.6 kg) 1.5 mL 2.0 mL

50 lb. (22.7 kg) 1/2 tsp 3/4 tsp

75 lb. (34 kg) 3/4 tsp 1 tsp

100 lb. (45.4kg) 1 tsp 1 1/2 tsp

OVERDOSAGE:

The signs and symptoms of overdose are headache, nausea, vomiting, blurred vision, dilated pupils, hot and dry skin, dizziness, dryness of the mouth, difficulty in swallowing, CNS stimulation. Treatment should consist of gastric lavage, emetics and activated charcoal. If indicated, parenteral cholinergic agents such as physostigmine or bethanechol chloride, should be added.

HOW SUPPLIED:

Phenobarbital with Belladonna Alkaloids Elixir is supplied as a purple colored, grape flavored liquid.

4 oz. bottles

NDC: 42291-205-04

16 oz. (Pint) bottles

NDC: 42291-205-16

AVOID FREEZING

Store at 20° – 25° C (68°- 77°F) [See USP Controlled Room Temperature]. Protect from light and moisture. Dispense in a tight, light-resistant container as defined in the USP, using a child-resistant closure.

All prescriptions using this product shall be pursuant to State statutes as applicable. This is not an Orange Book product. This product may be administered only under a physician’s supervision. There are no implied or explicit claims on the therapeutic equivalence.

WARNINGS: KEEP THIS AND ALL DRUGS OUT OF THE REACH OF CHILDREN. IN CASE OF ACCIDENTAL OVERDOSE, SEEK PROFESSIONAL ASSISTANCE OR CONTACT A POISON CONTROL CENTER IMMEDIATELY.

Manufactured for:

AvKARE

Pulaski, TN 38478

Mfg. Rev. 01/18

AV 05/20 (P)